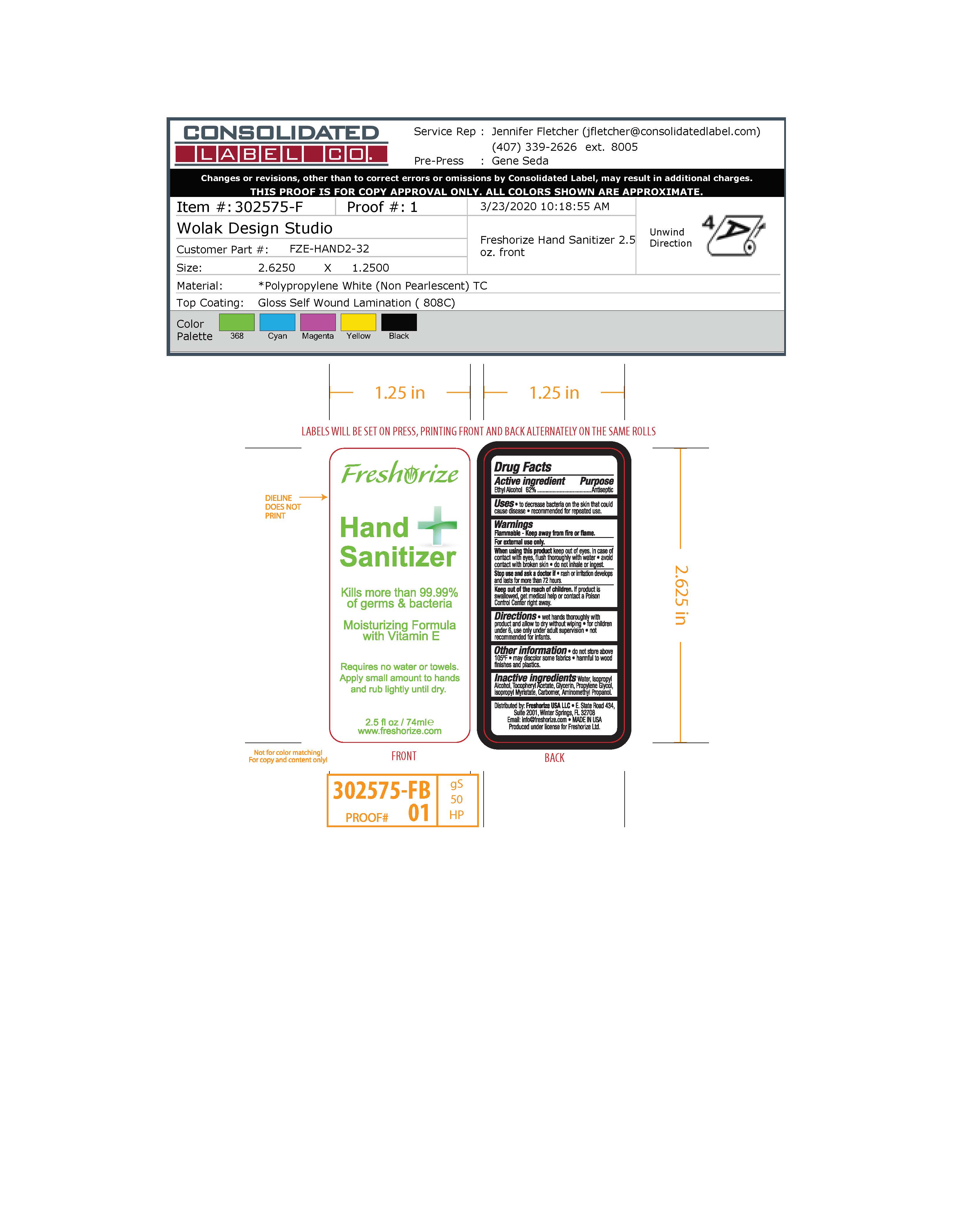 DRUG LABEL: United Airlines
NDC: 52305-223 | Form: GEL
Manufacturer: Freshorize Ltd.
Category: otc | Type: HUMAN OTC DRUG LABEL
Date: 20200708

ACTIVE INGREDIENTS: ALCOHOL 65.3 mL/100 mL
INACTIVE INGREDIENTS: ISOPROPYL MYRISTATE 1.5 mL/100 mL; CARBOMER HOMOPOLYMER, UNSPECIFIED TYPE 2.5 mL/100 mL; GLYCERIN 3.5 mL/100 mL; PROPYLENE GLYCOL 1.5 mL/100 mL; ISOPROPYL ALCOHOL 5 mL/100 mL; .ALPHA.-TOCOPHEROL ACETATE 0.5 mL/100 mL; AMINOMETHYLPROPANOL 1.5 mL/100 mL; WATER 18.7 mL/100 mL

United Airlines Gel Hand Sanitizer.DCR

Uses:

To decrease bacteria on the skin that could cause disease. Recommended for repeated use.

Warnings:

Flammable - Keep away from fire or flame
For external use only.
When using this product keep out of eyes. In case of contact with eyes, flush thoroughly with water.
Avoid contact with broken skin.
Do not inhale or ingest
Stop use and ask doctor is rash or irritation develops and lasts more than 72 hours.
If product is swallowed, get medical help or contact a Poison Control Center right away.

Warnings:

Keep out of the reach of children.

Directions:

Wet hands thoroughly with product and allow to dry without wiping. For children under 6, use only under adult supervision.

Not recommended for infants.

Other information:

Do not store above 105°
May discolor some fabrics
Harmful to wood finish and plastics.

Drug Facts

Active ingredient: Ethyl Alcohol 62%

Purpose

Antiseptic

Inactive ingredients:

Water, Isopropyl Alcohol, Tocopheryl Acetate, Glycerin, Propylene Glycol, Isopropyl Myristate, Carbomer, Aminomethyl Propanol

Brand Label

Front Label

Requires no water or towels.
Apply small amount to hands and rub lightly until dry.